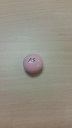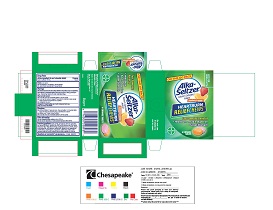 DRUG LABEL: Assorted Fruit Panned
NDC: 52642-229 | Form: TABLET, CHEWABLE
Manufacturer: BestCo Inc
Category: otc | Type: HUMAN OTC DRUG LABEL
Date: 20160216

ACTIVE INGREDIENTS: CALCIUM CARBONATE 750 mg/1 1
INACTIVE INGREDIENTS: CARNAUBA WAX

Calcium Carbonate 750mg

ACTIVE INGREDIENT

Calcium Carbonate 750mg

Purpose

Antacid

INDICATIONS AND USAGE

Uses for the relief of:

- acid indigestion
- heartburn
- sour stomach
- upset stomach associated with these symptoms

Warnings

Do not use if you have ever had an allergic reaction to this product or any of its ingredients

Ask a doctor or pharmacist before use if you are presently taking a prescription drug. Antacids may interact with certian prescription drugs.

When using this product

- do not take more than 5 chewable tablets in a 24-hour period
- do not use the maximum dosage of this product for more htan 2 weeks except under the advice and supervision of a physician.
- constipation may occur

PREGNANCY OR BREAST FEEDING

If pregnant or breast-feeding, ask a health professional before use.

Keep out of reach of children.

Directions

- adults and children 12 years and over: chew and swallow 1-2 chewable tablets every 2-4 hours as symptoms occur, or as directed by a doctor
- children under 12 years: consult a doctor
- do not take more than 5 chewable tablets in a 24-hour period

Other Information

- each chewable tablet contains: calcium 300 mg
- store at room temperature. Avoid excessive heat above 40C (104F).

Inactive Ingredients

acacia, carmine, carnauba wax, citric acid, corn starch, corn syrup, FD&C blue #1 aluminum lake, FD&C red #40 aluminum lake, FD&C yellow #6 aluminum lake, FD&C yellow #6, flavors, hydrogenated coconut oil, lecithin, medium chain triglycerides, methly paraben, modified starch, phosporic acid, pregelatinized modified starch, propylene glycol, propyl paraben, purified water, shellac, sodium benozate, sorbic acid, sorbitol, sucrose, titanium dioxide, begetable oil, white wax